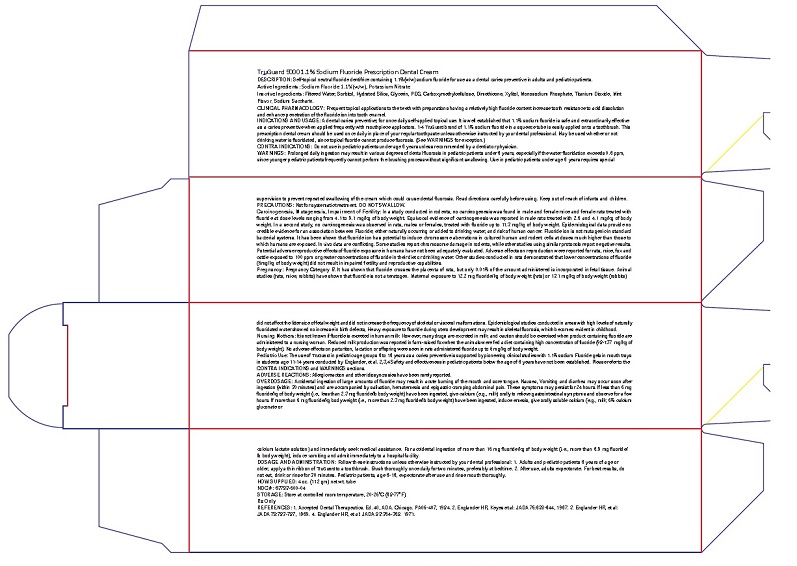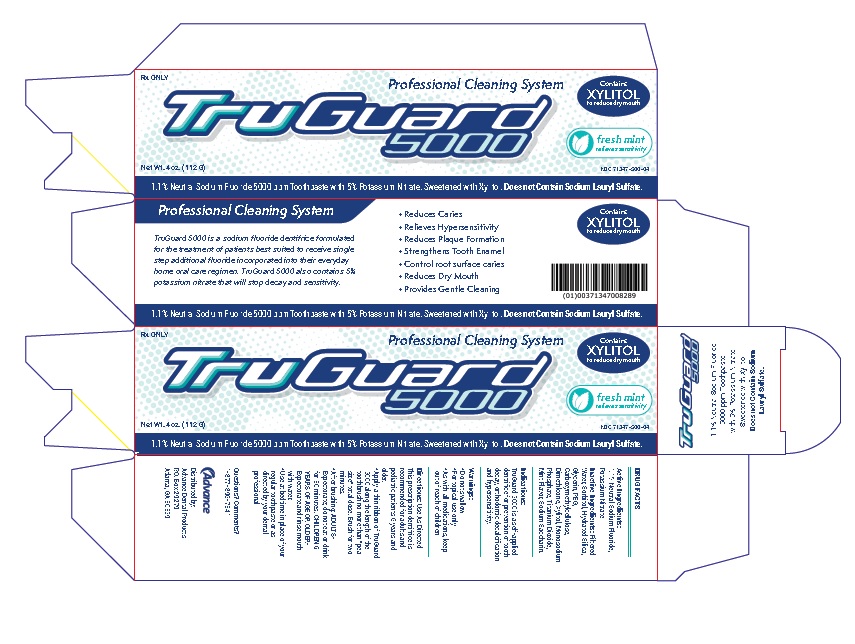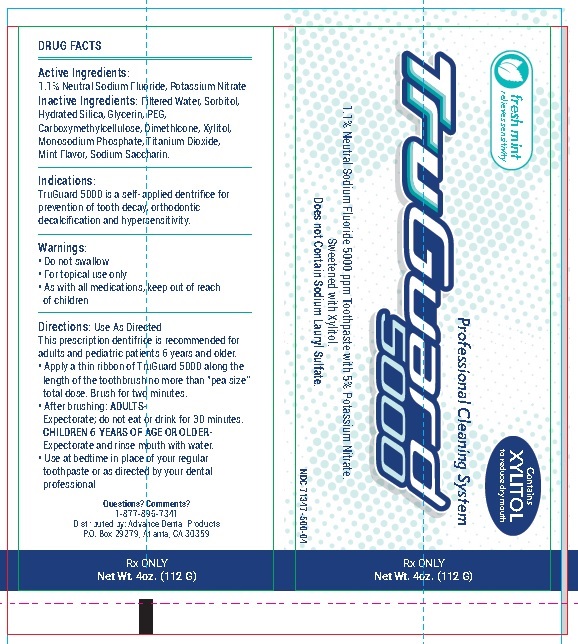 DRUG LABEL: TruGuard 5000
NDC: 71347-500 | Form: PASTE, DENTIFRICE
Manufacturer: The Atlanta Dental Supply Company DBA Advanced Dental Products
Category: prescription | Type: HUMAN PRESCRIPTION DRUG LABEL
Date: 20241228

ACTIVE INGREDIENTS: SODIUM FLUORIDE 1.1 g/100 g; POTASSIUM NITRATE 5.0 g/100 g
INACTIVE INGREDIENTS: WATER; SORBITOL; HYDRATED SILICA; GLYCERIN; POLYETHYLENE GLYCOL, UNSPECIFIED; CARBOXYMETHYLCELLULOSE; DIMETHICONE; XYLITOL; SODIUM PHOSPHATE, MONOBASIC, MONOHYDRATE; TITANIUM DIOXIDE; SACCHARIN SODIUM

TruGuard 5000 Professional Cleaning System

TruGuard 5000 1.1% Sodium Fluoride Prescription Toothpaste

Rx Only

DESCRIPTION

DESCRIPTION: Self-topical neutral fluoride dentifrice containing 1.1%(w/w) sodium fluoride for use as a dental caries preventive in adults and pediatric patients.

Active Ingredients: Sodium Fluoride 1.1%(w/w), Potassium Nitrate

INACTIVE INGREDIENT

Inactive Ingredients: Filtered Water, Sorbitol, Hydrated Silica, Glycerin, PEG, Carboxymethylcellulose, Dimethicone, Xylitol, Monosodium Phosphate, Titanium Dioxide, Mint Flavor, Sodium Saccharin.

CLINICAL PHARMACOLOGY

CLINICAL PHARMACOLOGY: Frequent topical applications to the teeth with preparations having a relatively high fluoride content increase tooth resistance to acid dissolutionand enhance penetration of the fluoride ion into tooth enamel.

INDICATIONS AND USAGE: A dental caries preventive; for once daily self-applied topical use. It is well established that 1.1% sodium fluoride is safe and extraordinarily effective as a caries preventive when applied frequently with mouthpiece applicators. 1-4 TruGuard brand of 1.1% sodium fluoride in a squeeze tube is easily applied onto a toothbrush. This prescription dental cream should be used once daily in place of your regular toothpaste unless otherwise instructed by your dental professional. May be used whether or not drinking water is fluoridated, since topical fluoride cannot produce fluorosis. (See WARNINGS for exception.)

CONTRAINDICATIONS

CONTRA INDICATIONS: Do not use in pediatric patients under age 6 years unless recommended by a dentist or physician.

WARNINGS

WARNINGS: Prolonged daily ingestion may result in various degrees of dental fluorosis in pediatric patients under 6 years, especially if the water fluoridation exceeds 0.6 ppm, since younger pediatric patients frequently cannot perform the brushing process without significant swallowing. Use in pediatric patients under age 6 years requires special supervision to prevent repeated swallowing of the cream which could cause dental fluorosis. Read directions carefully before using. Keep out of reach of infants and children.

PRECAUTIONS: Not for systematic treatment. DO NOT SWALLOW.

CARCINOGENESIS AND MUTAGENESIS AND IMPAIRMENT OF FERTILITY

Carcinogenesis, Mutagenesis, Impairment of Fertility: In a study conducted in rodents, no carcinogenesis was found in male and female mice and female rats treated with fluoride at dose levels ranging from 4.1 to 9.1 mg/kg of body weight. Equivocal evidence of carcinogenesis was reported in male rats treated with 2.5 and 4.1 mg/kg of bodyweight. In a second study, no carcinogenesis was observed in rats, males or females, treated with fluoride up to 11.3 mg/kg of body weight. Epidemiological data provide no credible evidence for an association between Fluoride; either naturally occurring or added to drinking water, and risk of human cancer. Fluoride ion is not mutagenic in standard bacterial systems. It has been shown that fluoride ion has potential to induce chromosome aberrations in cultured human and rodent cells at doses much higher than those to which humans are exposed. In vivo data are conflicting. Some studies report chromosome damage in rodents, while other studies using similar protocols report negative results.
Potential adverse reproductive effects of fluoride exposure in humans have not been adequately evaluated. Adverse effects on reproduction were reported for rats, mice, fox and cattle exposed to 100 ppm or greater concentrations of fluoride in their diet or drinking water. Other studies conducted in rats demonstrated that lower concentrations of fluoride (5mg/kg of body weight) did not result in impaired fertility and reproductive capabilities.

PREGNANCY

Pregnancy: Pregnancy Category B. It has shown that fluoride crosses the placenta of rats, but only 0.01% of the amount administered is incorporated in fetal tissue. Animal studies (rats, mice, rabbits) have shown that fluoride is not a teratogen. Maternal exposure to 12.2 mg fluoride/kg of body weight (rats) or 13.1 mg/kg of body weight (rabbits) did not affect the litter size of fetal weight and did not increase the frequency of skeletal or visceral malformations. Epidemiological studies conducted in areas with high levels of naturally fluoridated water showed no increase in birth defects, Heavy exposure to fluoride during utero development may result in skeletal fluorosis, which becomes evident in childhood.

NURSING MOTHERS

Nursing Mothers: It is not known if fluoride is excreted in human milk. However, many drugs are excreted in milk, and caution should be exercised when product containing fluoride are administered to a nursing woman. Reduced milk production was reported in farm-raised fox when the animals were fed a diet containing high concentration of fluoride (98-137 mg/kg of body weight). No adverse effects on parturition, lactation or offspring were seen in rats administered fluoride up to 5 mg/kg of body weight.

PEDIATRIC USE

Pediatric Use: The use of TruGuard in pediatric age groups 6 to 16 years as a caries preventive is supported by pioneering clinical studies with 1.1% sodium Fluoride gels in mouth trays in students age 11-14 years conducted by Englander, et al. 2,3,4 Safety and effectiveness in pediatric patients below the age of 6 years have not been established. Please refer to the CONTRA INDICATIONS and WARNINGS sections.

ADVERSE REACTIONS

ADVERSE REACTIONS: Allergic reaction and other idiosyncrasies have been rarely reported.

OVERDOSAGE

OVERDOSAGE: Accidental ingestion of large amounts of fluoride may result in acute burning of the mouth and sore tongue. Nausea, Vomiting and diarrhea may occur soon after ingestion (within 30 minutes) and are accompanied by salivation, hematemesis and epigastric cramping abdominal pain. These symptoms may persist for 24 hours. If less than 5 mg fluoride/kg of body weight (i.e., less than 2.3 mg fluoride/lb body weight) have been ingested, give calcium (e.g., milk) orally to relieve gastrointestinal symptoms and observe for a few hours. If more than 5 mg fluoride/kg body weight (i.e., more than 2.3 mg fluoride/lb body weight) have been ingested, induce emesis, give orally soluble calcium (e.g., milk, 5% calcium gluconate or calcium lactate solution) and immediately seek medical assistance. For accidental ingestion of more than 15 mg fluoride/kg of body weight (i.e., more than 6.9 mg fluoride/lb body weight), induce vomiting and admit immediately to a hospital facility.

DOSAGE AND ADMINISTRATION: Follow these instructions unless otherwise instructed by your dental professional: 1. Adults and pediatric patients 6 years of age or older, apply a thin ribbon of TruGuard to a toothbrush. Brush thoroughly once daily for two minutes, preferably at bedtime. 2. After use, adults expectorate. For best results, do not eat, drink or rinse for 30 minutes. Pediatric patients, age 6-16, expectorate after use and rinse mouth thoroughly.

Directions: Use As Directed
This prescription dentifrice is
recommended for adults and
pediatric patients 6 years and
older.
• Apply a thin ribbon of TruGuard
5000 along the length of the
toothbrush no more than "pea
size” total dose. Brush for two
minutes.
• After brushing: ADULTS- Expectorate;
Expectorate; do not eat or drink
for 30 minutes. CHILDREN 6
YEARS OF AGE OR OLDER-Expectorate
Expectorate and rinse mouth
with water.
• Use at bedtime in place of your
regular toothpaste or as
directed by your dental
professional.

HOW SUPPLIED

HOW SUPPLIED: 4 oz. (112 gm) net wt. tube

OTHER SAFETY INFORMATION

STORAGE: Store at controlled room temperature, 20-25˚C (68-77˚F).

NDC #: 71347-500-04

PRINCIPAL DISPLAY PANEL - 4 OZ. TubeSodium Fluoride 1.1%(w/w), Potassium Nitrate Toothpaste

Rx Only NDC 71347-500-04

TruGuard 5000

Professional Cleaning Syatem

1.1% Neutral Sodium Fluoride 5000 ppm Toothpaste with 5% Potassium Nitrate. Sweetened with Xylitol. Does not Contain Sodium Lauryl Sulfate.

Net Wt. 4 oz. (112 G)

Distributed by:
Advanced Dental Products
P.O. Box 29279
Atlanta, GA 30359

Carton Label

Tube Label

res